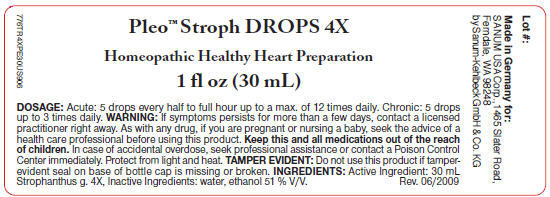 DRUG LABEL: Pleo Stroph
NDC: 60681-9011 | Form: SOLUTION/ DROPS
Manufacturer: Sanum Kehlbeck GmbH & Co. KG
Category: homeopathic | Type: HUMAN OTC DRUG LABEL
Date: 20091130

ACTIVE INGREDIENTS: strophanthus hispidus 4 [hp_X]/30 mL
INACTIVE INGREDIENTS: water; alcohol

Pleo™ Stroph
DROPS 4X

Homeopathic Preparation for a Healthy Heart

1 fl oz
(30 mL)

ACTIVE INGREDIENTS

30 mL Strophanthus g. 4X.

INACTIVE INGREDIENTS

water, ethanol 51% V/V

Tamper Evident

Do not use this product if tamper-evident seal on base of cap is missing or broken.

DOSAGE

Acute

5 drops every half to full hour up to a max. of 12 times daily.

Chronic

5 drops up to 3 times daily.

WARNING

If symptoms persist for more than a few days, contact a licensed practitioner right away. As with any drug, if you are pregnant or nursing a baby, seek the advice of a health care professional before using this product.

KEEP OUT OF REACH OF CHILDREN

Keep this and all medications out of the reach of children. In case of accidental overdose, seek professional assistance or contact a Poison Control Center immediately.

STORAGE AND HANDLING

Protect from light and heat.

Made in Germany.

Distributed by:
SANUM USA Corp.
1465 Slater Road
Ferndale, WA 98248

Manufactured By:
Sanum-Kehlbeck
GmbH & Co. KG

Rev. 08/2005

PRINCIPAL DISPLAY PANEL - 30 mL Label

Pleo™ Stroph DROPS 4X

Homeopathic Healthy Heart Preparation

1 fl oz (30 mL)

DOSAGE: Acute: 5 drops every half to full hour up to a max. of 12 times daily. Chronic: 5 drops
up to 3 times daily. WARNING: If symptoms persists for more than a few days, contact a licensed
practitioner right away. As with any drug, if you are pregnant or nursing a baby, seek the advice of a
health care professional before using this product. Keep this and all medications out of the reach
of children. In case of accidental overdose, seek professional assistance or contact a Poison Control
Center immediately. Protect from light and heat. TAMPER EVIDENT: Do not use this product if tamper-
evident seal on base of bottle cap is missing or broken. INGREDIENTS: Active Ingredient: 30 mL
Strophanthus g. 4X, Inactive Ingredients: water, ethanol 51 % V/V.
Rev. 06/2009